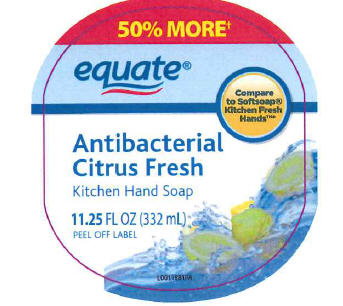 DRUG LABEL: Antibacterial Citrus Fresh
NDC: 49035-954 | Form: SOAP
Manufacturer: Wal-Mart Stores, Inc
Category: otc | Type: HUMAN OTC DRUG LABEL
Date: 20110404

ACTIVE INGREDIENTS: TRICLOSAN .115 kg/100 L
INACTIVE INGREDIENTS: WATER; SODIUM LAURETH SULFATE; SODIUM LAURYL SULFATE; COCAMIDOPROPYL BETAINE; METHYL GLUCETH-10; SODIUM CHLORIDE; SODIUM HYDROXIDE; BENZYL ALCOHOL; SHEA BUTTER; MANNITOL; MICA; TRIETHYL CITRATE; TITANIUM DIOXIDE

Drug Facts

Active ingredient
Triclosan (0.115%

Purpose
Antibacterial

INDICATIONS AND USAGE

Use for handwashing to decrease bacteria on the skin

Warnings
For external use only-hands only

When using this product
• do not get into eyes. If contact occurs, rinse eyes thoroughly with water.

Keep out of reach of children. If swallowed, get medical help or contact a Poison Control Center right away

DOSAGE AND ADMINISTRATION

Directions •wet hands •apply palmful to hands •scrub thoroughly •rinse

INACTIVE INGREDIENT

Inactive ingredients water, sodium laureth sulfate, sodium lauryl sulfate, acrylates copolymer, cocamidopropyl betaine, methyl gluceth-10, PPG-10 methyl glucose ether, fragrance, sodium chloride, cocamide MEA, sodium hydroxide, benzyl alcohol, butyrospermum parkii (shea butter), tetrasodium EDTA, mannitol, cellulose, mica, acrylates/ammonium methacrylate copolymer, triethyl citrate, citric acid, titanium dioxide, iron oxides, alumina, hydroxypropyl methylcellulose, yellow 5, red 33

50% more than the 7.5 FL OZ size
Made in the USA with US and foreign components
This product is not manufactured or distributed by Colgate-Polmolive Company, distributor of Softsoap Kitchen Fresh Hands Antibacterial Hand Soap

ADVERSE REACTIONS

Distributed by:
Wal-Mart Stores Inc.
Bentonville, AR 72716
Satisfaction quaranteed - Or we'll replace it or give you your
money back. For questions or comments or to report an
undesired reaction or side effect, please call 1-888-287-1915.

PACKAGE LABEL

50% MORE
equate
compare
to Softsoap
Kitchen Fresh
Hands
Antibacterial
Citrus Fresh
Kitchen Hand Soap
11.25 FL OZ (332 mL)
PEEL OFF LABEL